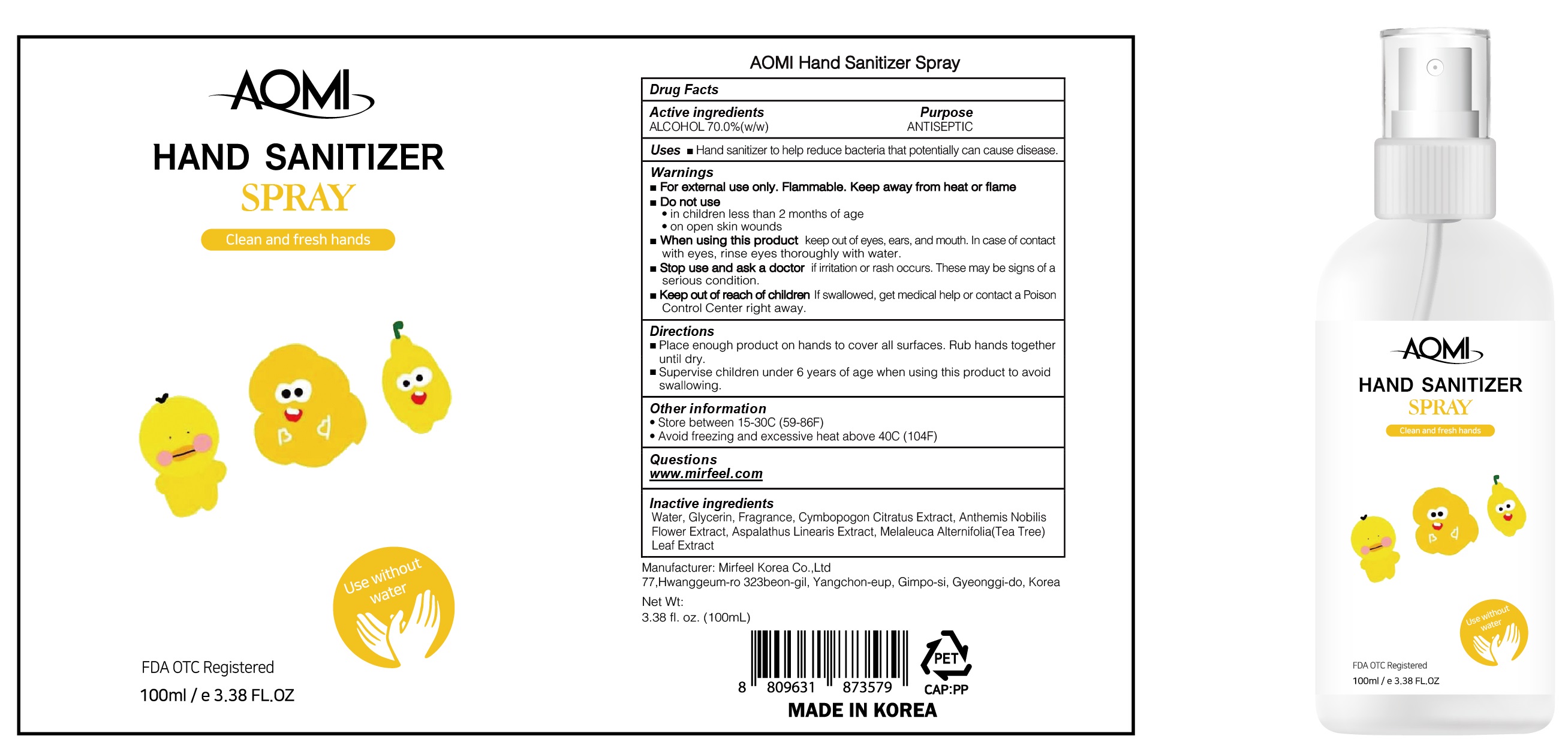 DRUG LABEL: AOMI HAND SANITIZER
NDC: 75010-040 | Form: SPRAY
Manufacturer: Mirfeel Korea Co., Ltd
Category: otc | Type: HUMAN OTC DRUG LABEL
Date: 20200604

ACTIVE INGREDIENTS: Alcohol 70 g/100 mL
INACTIVE INGREDIENTS: Water; Glycerin; CHAMAEMELUM NOBILE FLOWER; MELALEUCA ALTERNIFOLIA LEAF

ACTIVE INGREDIENT

ALCOHOL 70.0% (w/w)

INACTIVE INGREDIENT

Water, Glycerin, Fragrance, Cymbopogon Citratus Extract, Anthemis Nobilis Flower Extract, Aspalathus Linearis Extract, Melaleuca Alternifolia(Tea Tree)Leaf Extract

PURPOSE

ANTISEPTIC

WARNINGS

For external use only. Flammable. Keep away from heat or flame
--------------------------------------------------------------------------------------------------------
Do not use
• in children less than 2 months of age
• on open skin wounds
--------------------------------------------------------------------------------------------------------
When using this product keep out of eyes, ears, and mouth. In case of contact with eyes, rinse eyes thoroughly with water.
--------------------------------------------------------------------------------------------------------
Stop use and ask a doctor if irritation or rash occurs. These may be signs of a serious condition.

KEEP OUT OF REACH OF CHILDREN

If swallowed, get medical help or contact a Poison Control Center right away.

Uses

Hand sanitizer to help reduce bacteria that potentially can cause disease.

Directions

• Place enough product on hands to cover all surfaces. Rub hands together until dry.
• Supervise children under 6 years of age when using this product to avoid swallowing.

Other Information

• Store between 15-30C (59-86F)
• Avoid freezing and excessive heat above 40C (104F)

QUESTIONS

www.mirfeel.com